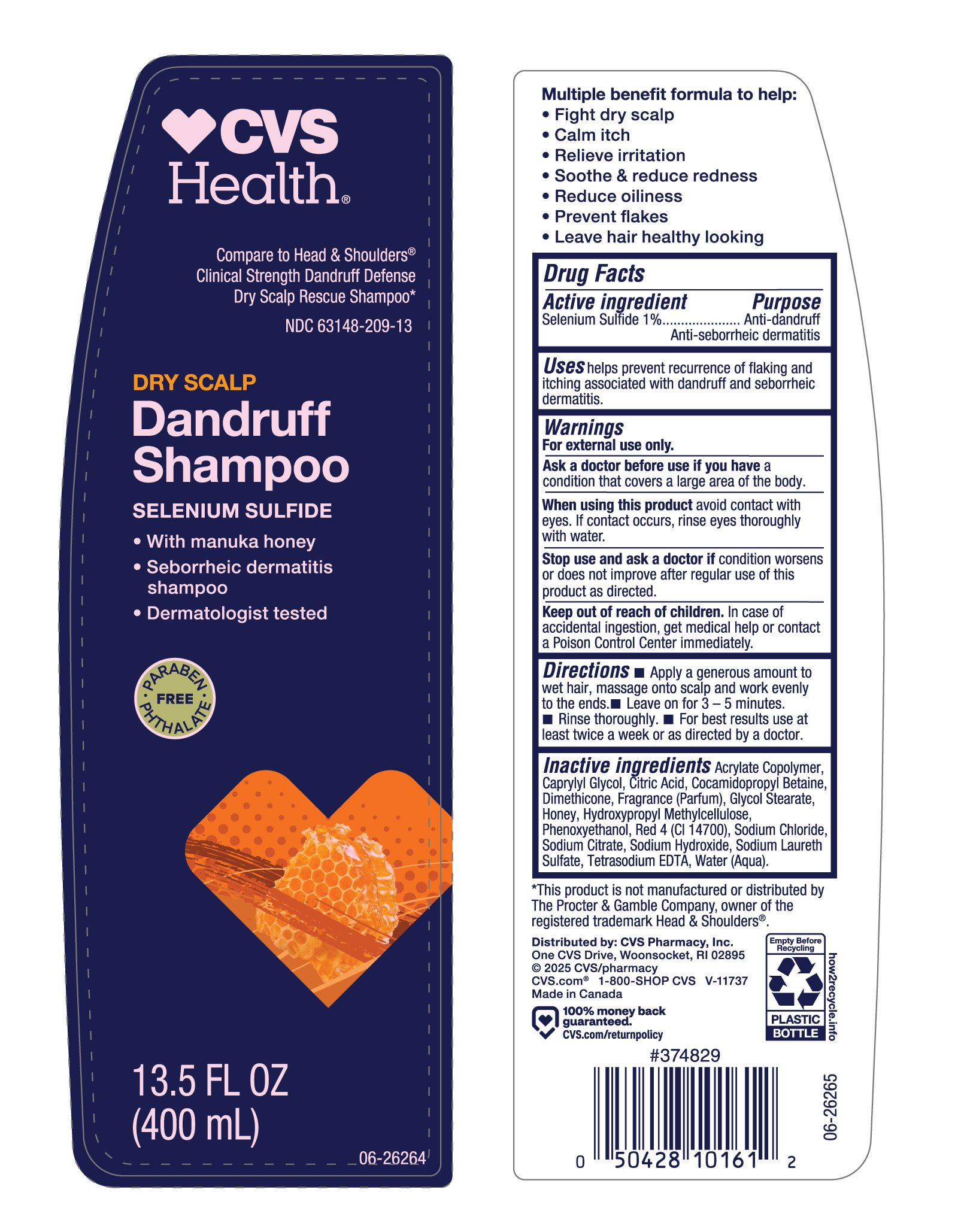 DRUG LABEL: CVS Gold
NDC: 63148-209 | Form: SHAMPOO
Manufacturer: Apollo Health and Beauty Care
Category: otc | Type: HUMAN OTC DRUG LABEL
Date: 20241215

ACTIVE INGREDIENTS: SELENIUM SULFIDE 1000 mg/100 mL
INACTIVE INGREDIENTS: WATER; CITRIC ACID; DIMETHICONE; FRAGRANCE CLEAN ORC0600327; SODIUM HYDROXIDE; COCAMIDOPROPYL BETAINE; RED 4; TETRASODIUM EDTA; ACRYLATES/VINYL ISODECANOATE CROSSPOLYMER (10000 MPA.S NEUTRALIZED AT 0.5%); HONEY; SODIUM CHLORIDE; SODIUM CITRATE; SODIUM LAURETH SULFATE; PHENOXYETHANOL; GLYCOL STEARATE; CAPRYLYL GLYCOL; HYDROXYPROPYL METHYLCELLULOSE

63148-209, CVS Dandruff Shampoo- Dry Scalp

Active Ingredient

Selenium Sulfide 1%

Purpose

Anti-dandruff Anti-seborrheic dermatitis

Uses

Helps prevent recurrence of flaking and itching associated with dandruff and seborrheic dermatitis.

Warnings

For external use only

Ask a doctor before use if you have a condition that covers a large area of the body.

When using this product avoid contact with eyes. If contact occurs, rinse eyes thoroughly with water.

Stop use and ask a doctor if condition worsens or does not improve after regular use of this product as directed.

Keep out of reach of children. In case of accidental ingestion, get medical help or contact a Poison Control Center immediately.

Directions

- Apply a generous amount to wet hair, massage onto scalp and work evenly to the ends.
- Leave on for 3-5 minutes.
- Rinse thoroughly.
- For best results use at least twice a week or as directed by a doctor.

Inactive Ingredients

Acrylate Copolymer, Caprylyl Glycol, Citric Acid, Cocamidopropyl Betaine, Dimethicone, Fragrance (Parfum), Glycol Stearate, Honey, Hydroxypropyl Methylcellulose, Phenoxyethanol, Red 4 (CI 14700), Sodium Chloride, Sodium Citrate, Sodium Hydroxide, Sodium Laureth Sulfate, Tetrasodium EDTA, Water (Aqua).